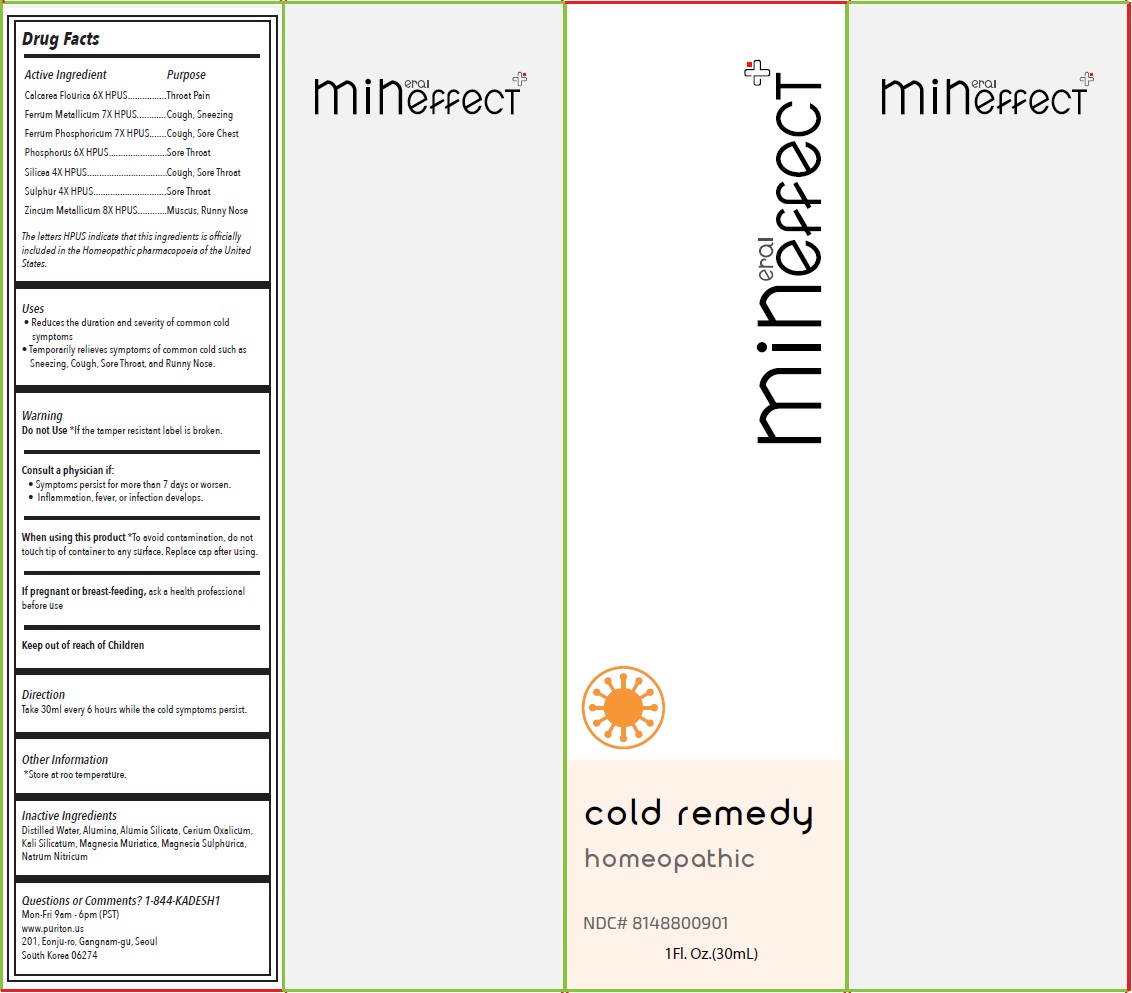 DRUG LABEL: Mineffect cold remedy
NDC: 81488-009 | Form: LIQUID
Manufacturer: Kadesh Incoporation Co,Ltd
Category: homeopathic | Type: HUMAN OTC DRUG LABEL
Date: 20231031

ACTIVE INGREDIENTS: CALCIUM FLUORIDE 6 [hp_X]/30 mL; IRON 7 [hp_X]/30 mL; FERROSOFERRIC PHOSPHATE 7 [hp_X]/30 mL; PHOSPHORUS 6 [hp_X]/30 mL; SILICON DIOXIDE 4 [hp_X]/30 mL; SULFUR 4 [hp_X]/30 mL; ZINC 8 [hp_X]/30 mL
INACTIVE INGREDIENTS: WATER; ALUMINUM OXIDE; KAOLIN; CEROUS OXALATE NONAHYDRATE; POTASSIUM SILICATE; MAGNESIUM CHLORIDE; MAGNESIUM SULFATE HEPTAHYDRATE; SODIUM NITRATE

Mineffect cold remedy

Active Ingredient

Calcarea Flourica 6X HPUS
Ferrum Metallicum 7X HPUS
Ferrum Phosphoricum 7X HPUS
Phosphorus 6X HPUS
Silicea 4X HPUS
Sulphur 4X HPUS
Zincum Metallicum 8X HPUS

Purpose

Throat Pain
Cough, Sneezing
Cough, Sore Chest
Sore Throat
Cough, Sore Throat
Sore Throat
Muscus, Runny Nose

The letters HPUS indicate that this ingredients is officially included in the Homeopathic pharmacopoeia of the United States.

Uses

• Reduces the duration and severity of common cold symptoms
• Temporarily relieves symptoms of common cold such as Sneezing, Cough, Sore Throat, and Runny Nose.

Warning

Do not Use*If the tamper resistant label is broken.

Consult a physician if:
• Symptoms persist for more than 7 days or worsen.
• Inflammation, fever, or infection develops.

When using this product*To avoid contamination, do not touch tip of container to any surface. Replace cap after using.

If pregnant or breast-feeding, ask a health professional before use

Keep out of reach of Children

Direction

Take 30ml every 6 hours while the cold symptoms persist.

Other Information

*Store at room temperature.

Inactive Ingredients

Distilled Water, Alumina, Alumina Silicata, Cerium Oxalicum, Kali Silicatum, Magnesia Muriatica, Magnesia Sulphurica, Natrum Nitricum

Questions or Comments?

1-844-KADESH1

Mon-Fri 9am - 6pm (PST)
www.puriton.us
201, Eonju-ro, Gangnam-gu, Seoul
South Korea 06274

homeopathic